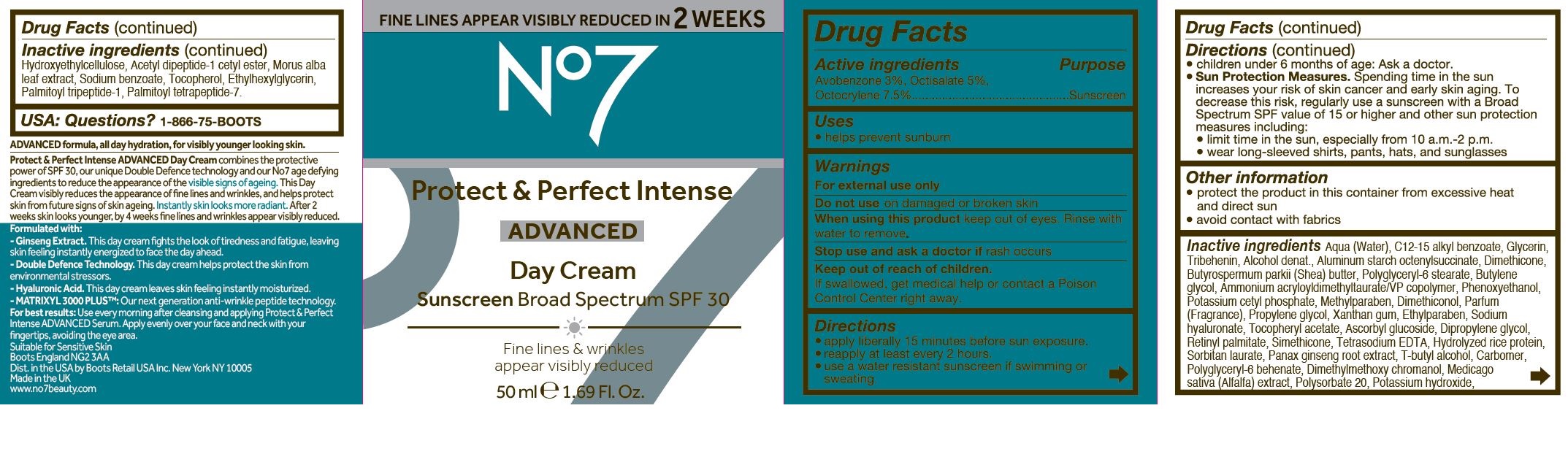 DRUG LABEL: No7 Protect and Perfect Intense Advanced Day Cream SPF 30
NDC: 61589-0250 | Form: CREAM
Manufacturer: BCM Cosmetique SAS
Category: otc | Type: HUMAN OTC DRUG LABEL
Date: 20250411

ACTIVE INGREDIENTS: AVOBENZONE 1.5 g/50 g; OCTOCRYLENE 3.75 g/50 g; OCTISALATE 2.5 g/50 g
INACTIVE INGREDIENTS: WATER; ALKYL (C12-15) BENZOATE; GLYCERIN; TRIBEHENIN; ALCOHOL; ALUMINUM STARCH OCTENYLSUCCINATE; DIMETHICONE; SHEA BUTTER; POLYGLYCERYL-6 STEARATE; BUTYLENE GLYCOL; AMMONIUM ACRYLOYLDIMETHYLTAURATE/VP COPOLYMER; PHENOXYETHANOL; POTASSIUM CETYL PHOSPHATE; METHYLPARABEN; DIMETHICONOL (40 CST); PROPYLENE GLYCOL; XANTHAN GUM; ETHYLPARABEN; HYALURONATE SODIUM; ALPHA-TOCOPHEROL ACETATE; ASCORBYL GLUCOSIDE; DIPROPYLENE GLYCOL; VITAMIN A PALMITATE; SILICON DIOXIDE; EDETATE SODIUM; SORBITAN MONOLAURATE; PANAX GINSENG ROOT OIL; TERT-BUTYL ALCOHOL; CARBOMER HOMOPOLYMER, UNSPECIFIED TYPE; POLYGLYCERYL-6 BEHENATE; DIMETHYLMETHOXY CHROMANOL; MEDICAGO SATIVA LEAF; POLYSORBATE 20; POTASSIUM HYDROXIDE; PALMITOYL TETRAPEPTIDE-7; HYDROXYETHYL CELLULOSE, UNSPECIFIED; PALMITOYL TRIPEPTIDE-1; N-ACETYL DIPEPTIDE-1; MORUS ALBA LEAF; SODIUM BENZOATE; TOCOPHEROL; ETHYLHEXYLGLYCERIN

No7 Protect and Perfect Intense Advanced Day Cream Sunscreen Broad Spectrum SPF 30

Carton Active Ingredients Section

Active ingredients

Avobenzone 3%

Octisalate 5%

Octocrylene 7.5%

Uses

Uses - helps prevent sunburn

Warnings

For external use only

Do not use on damaged or broken skin

When using this product keep out of eyes. Rinse with water to remove.

Warnings

For external use only

Do not use on damaged or broken skin

When using this product keep out of eyes. Rinse with water to remove.

Ask a doctor

Stop use and ask a doctor if rash occurs

Keep out of reach of children

If swallowed, get medical help or contact a Poison Control Center right away

Directions

apply liberally 15 minutes before sun exposure.

reapply at least every 2 hours.

use a water resistant sunscreen if swimming or sweating.

children under 6 months of age: Ask a doctor.

Sun Protection Measures. Spending time in the sun increases your risk of skin cancer and early skin aging. To decrease this risk, regularly use a sunscreen with a Broad Spectrum SPF value of 15 or higher and other sun protection measures including:

limit time in the sun, especially from 10 a.m-2 p.m.

wear long-sleeved shirts, pants, hats and sunglasses

Directions

apply liberally 15 minutes before sun exposure.

reapply at least every 2 hours.

use a water resistant sunscreen if swimming or sweating.

children under 6 months of age: Ask a doctor.

Sun Protection Measures. Spending time in the sun increases your risk of skin cancer and early skin aging. To decrease this risk, regularly use a sunscreen with a Broad Spectrum SPF value of 15 or higher and other sun protection measures including:

limit time in the sun, especially from 10 a.m-2 p.m.

wear long-sleeved shirts, pants, hats and sunglasses

Storage

Other information

protect the product in this container from excessive heat and direct sun

avoid contact with fabrics

Inactive ingredients

Aqua (Water), C12-15 alkyl benzoate, Glycerin, Tribehenin, Alcohol denat., Aluminum starch octenylsuccinate, Dimethicone, Butyrospermum parkii (Shea) butter, Polyglyceryl-6 stearate, Butylene glycol, Ammonium acryloydimethyltaurate/VP copolymer, Phenoxyethanol, Potassium cetyl phosphate, Methylparaben, Dimethiconol, Parfum(Fragrance), Propylene glycol, Xanthan gum, Ethylparaben, Sodium hyaluronate, Tocopheryl acetate, Ascorbyl glucoside, Dipropylene glycol, Retinyl palmitate, Simethicone, Tetrasodium EDTA, Hydolyzed rice protein, Sorbitan laurate, Panax gingseng root extract, T-butyl alcohol, Carbomer, Polyglyceryl-6 benhenate, Dimethylmethoxy chromanol, Medicago sativa (Alfalfa) extract, Polyosorbate 20, Potassium hydroxide, Hydroxyethylcelulose, Acetyl dipeptide-1 cetyl ester, Morus alba leaf extract, Sodium benzoate, Tocopherol, Ethylhexylglycerin, Palmitoyl tripeptide-1, Palmitoyl tetrapeptide-7.

PATIENT COUNSELING INFORMATION

USA: Questions? 1-866-75-BOOTS

The Boots Company PLC Nottingham England NG2 3AA

Boots Retail Ireland Dublin 12 Ireland

Dist. in the USA by Boots Retail USA Inc. New York NY 10005

Made in the UK

www.no7beauty.com

Description

FINE LINES APPEAR VISIBLY REDUCED IN 2 WEEKS

No7 Protect & Perfect Intense ADVANCED Day Cream Sunscreen Broad Spectrum SPF 30

Fine lines & wrinkles appear visibly reduced

50 ml e 1.69 US Fl. Oz.

ADVANCED formula, all day hydration, for visibly younger looking skin.

Protect & Perfect Intense ADVANCED Day Cream combines the protective power of SPF 30, our unique Double Defence technology and our No7 age defying ingredients to reduce the appearance of the visible signs of ageing. This Day Cream visibly reduced the appearance of fine lines and wrinkles, and helps protect skin from future signs of ageing. instantly skin looks more radiant. After 2 weeks skin looks younger, by 4 weeks fine lines and wrinkles appear visibly reduced.

Formulated with:

- Ginseng Extract. This day cream fights the look of tiredness and fatigue, leaving skin feeling instantly energized to face the day ahead.

- Double Defence Technology. This day cream helps protect the skin from environmental stressors.

- Hyaluronic Acid. This day cream leaves skin feeling instantly moisturized.

- MATRIXYL 3000 PLUS: Our next generation anti-wrinkle peptide technology.

For best results: Use every morning after cleansing and applying Protect & Perfect Intense ADVANCED Serum. Apply evenly over your face and neck with your fingertips, avoiding the eye area.

Suitable for Sensitive Skin